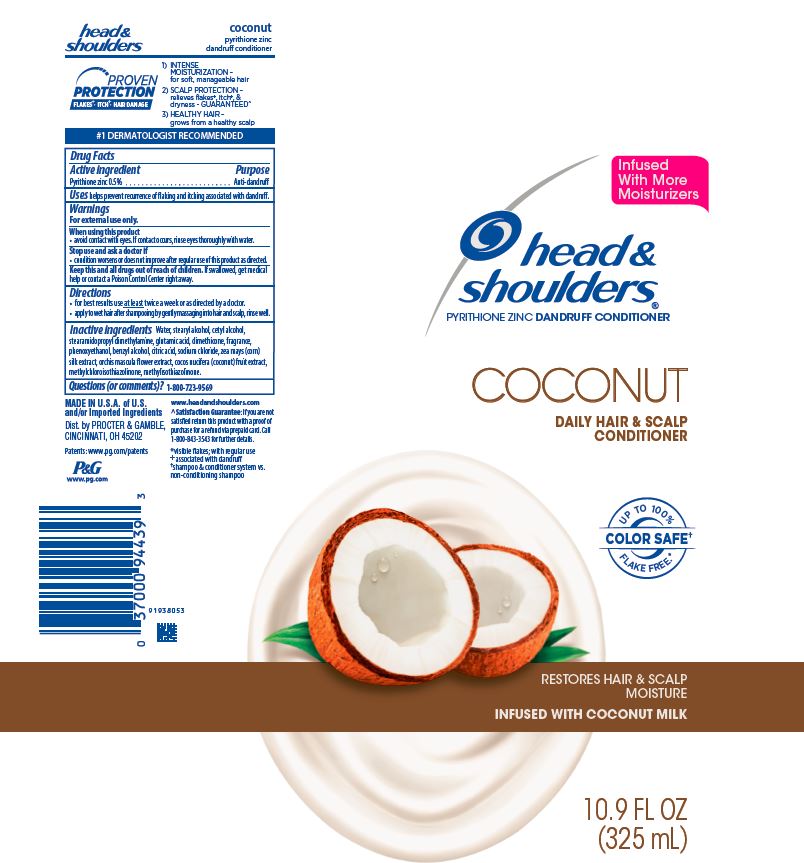 DRUG LABEL: Head and Shoulders Coconut
NDC: 69423-319 | Form: LOTION
Manufacturer: The Procter & Gamble Manufacturing Company
Category: otc | Type: HUMAN OTC DRUG LABEL
Date: 20251218

ACTIVE INGREDIENTS: PYRITHIONE ZINC 0.5 g/100 mL
INACTIVE INGREDIENTS: COCONUT; WATER; STEARYL ALCOHOL; CETYL ALCOHOL; STEARAMIDOPROPYL DIMETHYLAMINE; GLUTAMIC ACID; DIMETHICONE; PHENOXYETHANOL; BENZYL ALCOHOL; CITRIC ACID MONOHYDRATE; SODIUM CHLORIDE; CORN SILK; METHYLCHLOROISOTHIAZOLINONE; METHYLISOTHIAZOLINONE; ORCHIS MASCULA FLOWER

Head and Shoulders® Coconut Hair and Scalp Conditioner

Drug Facts

Active ingredient

Pyrithione zinc 0.5%

Purpose

Anti-dandruff

Uses

helps prevent recurrence of flaking and itching associated with dandruff.

Warnings

For external use only.

When using this product

- avoid contact with eyes. If contact occurs, rinse eyes thoroughly with water.

Stop use and ask a doctor if

- condition worsens or does not improve after regular use of this product as directed.

KEEP OUT OF REACH OF CHILDREN

Keep this and all drugs out of reach of children. If swallowed, get medical help or contact a Poison Control Center right away.

Directions

- for best results use at least twice a week or as directed by a doctor.
- apply to wet hair after shampooing by gently massaging into hair and scalp, rinse well.

Inactive ingredients

Water, stearyl alcohol, cetyl alcohol, stearamidopropyl dimethylamine, glutamic acid, dimethicone, fragrance, phenoxyethanol, benzyl alcohol, citric acid, sodium chloride, zea mays (corn) silk extract, orchis mascula flower extract, cocos nucifera (coconut) fruit extract, methylchloroisothiazolinone, methylisothiazolinone.

Questions (or comments)?

1-800-723-9569

Dist. by PROCTER & GAMBLE,
CINCINNATI, OH 45202

PRINCIPAL DISPLAY PANEL - 325 mL Tube Label

head &
shoulders®
pyrithione zinc dandruff conditioner

COCONUT

DAILY HAIR & SCALP

CONDITIONER

restores hair & scalp

moisture

infused with coconut milk

10.9 FL OZ (325 mL)